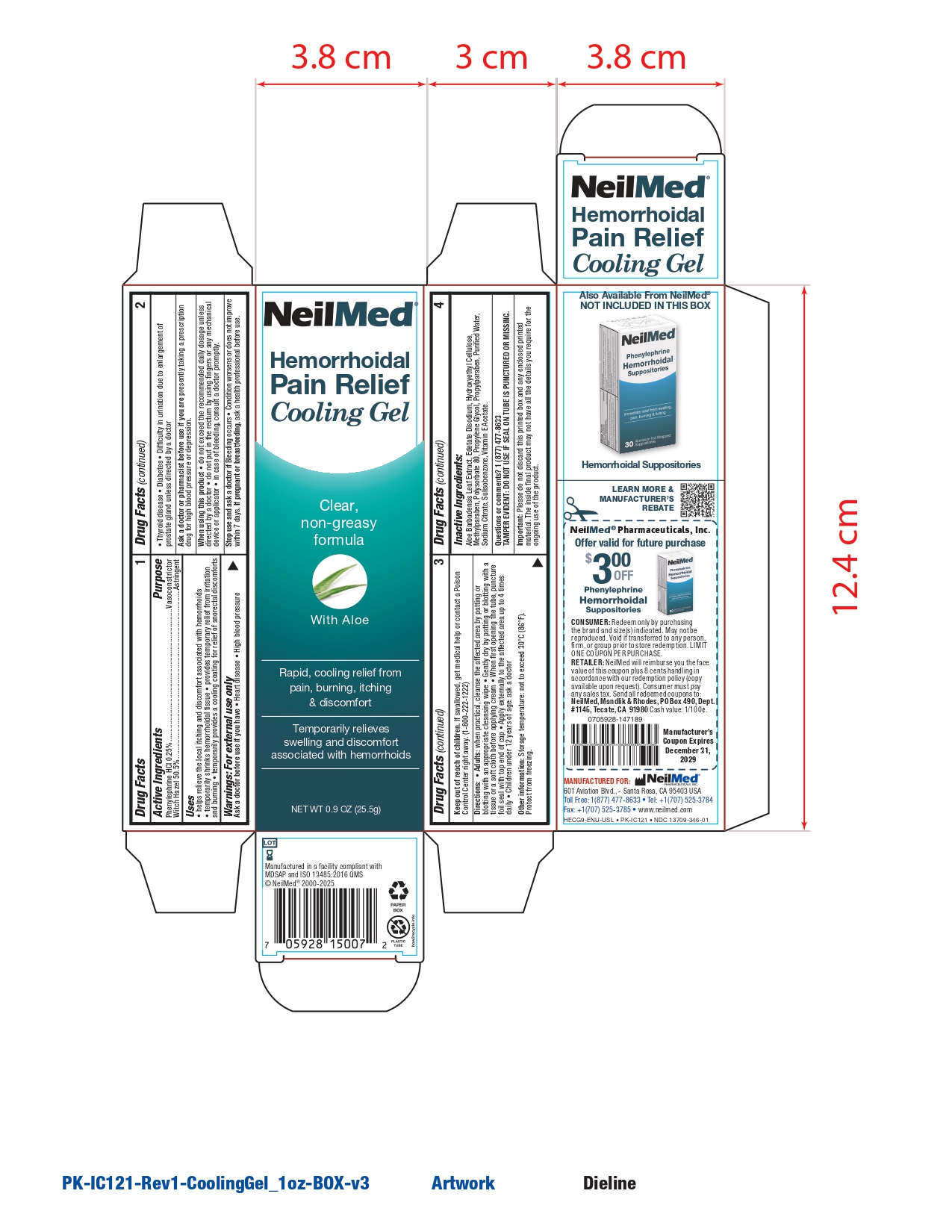 DRUG LABEL: Cooling Gel
NDC: 13709-346 | Form: GEL
Manufacturer: Neilmed Pharmaceuticals Inc.
Category: otc | Type: HUMAN OTC DRUG LABEL
Date: 20251113

ACTIVE INGREDIENTS: WITCH HAZEL 505 mg/1 g; PHENYLEPHRINE HYDROCHLORIDE 2.5 mg/1 g
INACTIVE INGREDIENTS: WATER; ALOE BARBADENSIS LEAF; METHYLPARABEN; EDETATE DISODIUM; PROPYLENE GLYCOL; PROPYLPARABEN; SODIUM CITRATE; SULISOBENZONE; ALPHA-TOCOPHEROL ACETATE; HYDROXYETHYL CELLULOSE (140 MPA.S AT 5%); POLYSORBATE 80

Cooling Gel

Drug Facts: Active Ingredients

Phenylephrine HCl 0.25%

Witch Hazel 50.5%

Purpose

Vasoconstrictor

Astringent

Uses

- helps relieve the local itching and discomfort associated with hemorrhoids
- temporarily shrinks hemorrhoidal tissue
- provides temporary relief from irritation and burning
- temporarily provides a cooling coating for relief of anorectal discomforts

Warnings

For External Use Only

Ask a doctor before use if you have

- heart disease
- high blood pressure
- diabetes
- thyroid disease
- difficulty in urination due to enlargement of the prostate gland unless directed by a doctor

Ask a doctor or pharmacist before use if you are

presently taking a prescription drug for high blood pressure or depression

When using this product

- do not exceed the recommended daily dosage unless directed by a doctor
- do not put in the rectum by using fingers or any mechanical device or applicator
- in case of bleeding, consult a doctor promptly

Stop use and ask a doctor if

condition worsens or does not improve within 7 days

If pregnant or breastfeeding,

ask a health professional before use.

Keep out of reach of children

If swallowed, get medical help or contact a Poison Control Center right away. (1-800-222-1222)

Directions

- Adults: When practical, cleanse the affected area by patting or blotting with an appropriate cleansing wipe
- Gently dry by patting or blotting with a tissue or soft cloth before applying gel
- When first opening the tube, puncture foil seal with the top end of the cap
- Apply externally to the affected area up to 4 times daily
- Children under 12 years of age: Ask a doctor

Other Information:

Storage temperature: not to exceed 30°C (86°F). Protect from freezing.

Inactive Ingredients:

Aloe barbadensis leaf extract, edetate disodium, hydroxyethyl cellulose, methylparaben, polysorbate 80, propylene glycol, propylparaben, purified water, sodium citrate, sulisobenzene, tocopheryl acetate (vitamin E).

Questions or Comments?

1-877-477-8633

TAMPER EVIDENT:

DO NOT USE IF SEAL ON TUBE IS PUNCTURED OR MISSING.

Important:

Please do not discard this printed box and any enclosed printed material. The inside final product may not have all the details you require for the ongoing use of the product